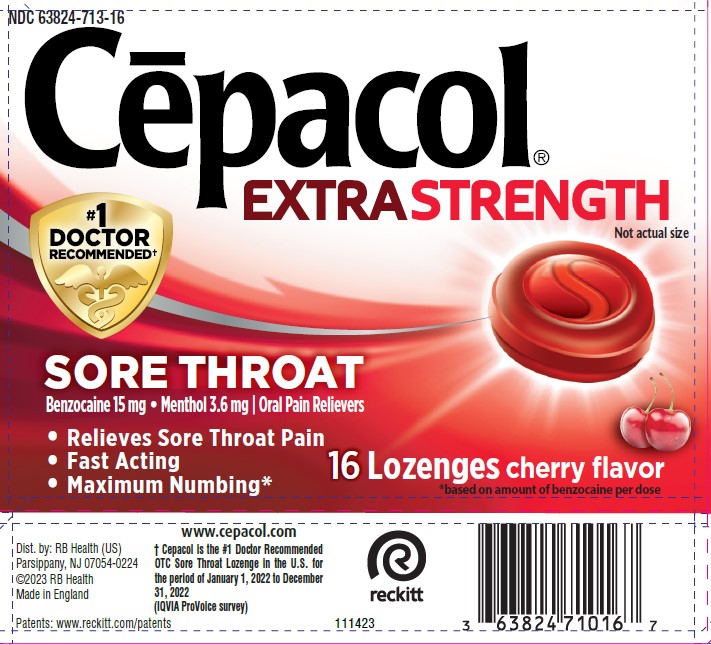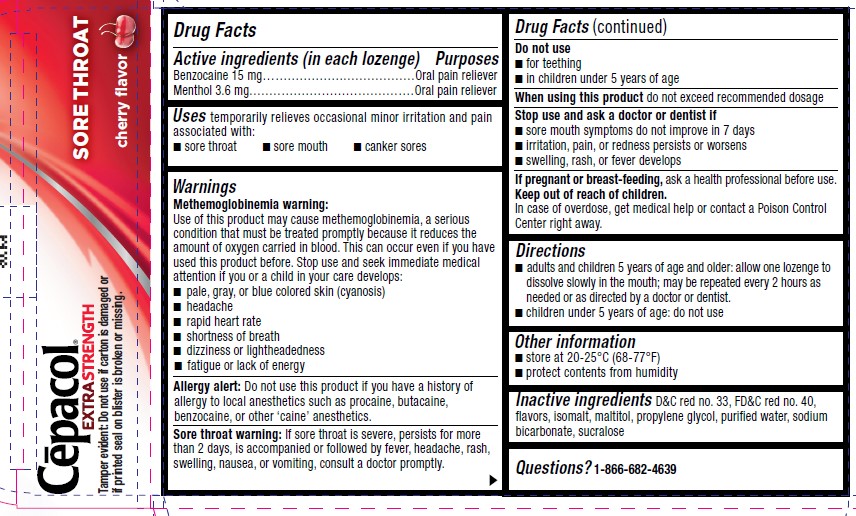 DRUG LABEL: Cepacol
NDC: 63824-713 | Form: LOZENGE
Manufacturer: RB Health (US) LLC
Category: otc | Type: HUMAN OTC DRUG LABEL
Date: 20250327

ACTIVE INGREDIENTS: BENZOCAINE 15 mg/1 1; MENTHOL, UNSPECIFIED FORM 3.6 mg/1 1
INACTIVE INGREDIENTS: D&C RED NO. 33; FD&C RED NO. 40; ISOMALT; MALTITOL; PROPYLENE GLYCOL; WATER; SODIUM BICARBONATE; SUCRALOSE

Cēpacol®
Extra Strength Sore Throat cherry

Drug Facts

ACTIVE INGREDIENT

PURPOSE

Active ingredients (in each lozenge) | Purposes
Benzocaine 15 mg | Oral pain reliever
Menthol 3.6 mg | Oral pain reliever

Uses

temporarily relieves occasional minor irritation and pain associated with:

- sore throat
- sore mouth
- canker sores

Warnings

Methemoglobinemia warning

Use of this product may cause methemoglobinemia, a serious condition that must be treated promptly because it reduces the amount of oxygen carried in blood. This can occur even if you have used this product before. Stop use and seek immediate medical attention if you or a child in your care develops:

- pale, gray, or blue colored skin (cyanosis)
- headache
- rapid heart rate
- shortness of breath
- dizziness or lightheadedness
- fatigue or lack of energy

Allergy alert

Do not use this product if you have a history of allergy to local anesthetics such as procaine, butacaine, benzocaine, or other ‘caine’ anesthetics.

Sore throat warning

If sore throat is severe, persists for more than 2 days, is accompanied or followed by fever, headache, rash, swelling, nausea, or vomiting, consult a doctor promptly.

Do not use

- for teething
- in children under 5 years of age

Stop use and ask a doctor or dentist if

- sore mouth symptoms do not improve in 7 days
- irritation, pain, or redness persists or worsens
- swelling, rash, or fever develops

PREGNANCY OR BREAST FEEDING

If pregnant or breast-feeding,ask a health professional before use.

Keep out of reach of children.

In case of overdose, get medical help or contact a Poison Control Center right away.

Do not exceed recommended dosage.

Directions

- adults and children 5 years of age and older: allow one lozenge to dissolve slowly in the mouth; may be repeated every 2 hours as needed or as directed by a doctor or dentist.
- children under 5 years of age: do not use

Other information

- store at 20-25°C (68-77°F)
- protect contents from humidity

Inactive ingredients

D&C red no. 33, FD&C red no. 40, flavors, isomalt, maltitol, propylene glycol, purified water, sodium bicarbonate, sucralose

Questions?

1-866-682-4639

Dist. by: RB Health (US)
Parsippany, NJ 07054-0224

Made in England

PRINCIPAL DISPLAY PANEL - 16 Lozenge Blister Pack Carton

NDC 63824-713-16

Cēpacol®
EXTRA STRENGTH

#1
DOCTOR
RECOMMENDED†

SORE THROAT
Benzocaine 15 mg • Menthol 3.6 mg | Oral Pain Relievers

- Relieves Sore Throat Pain
- Fast Acting
- Maximum Numbing*

16 Lozenges cherry flavor
*based on amount of benzocaine per dose